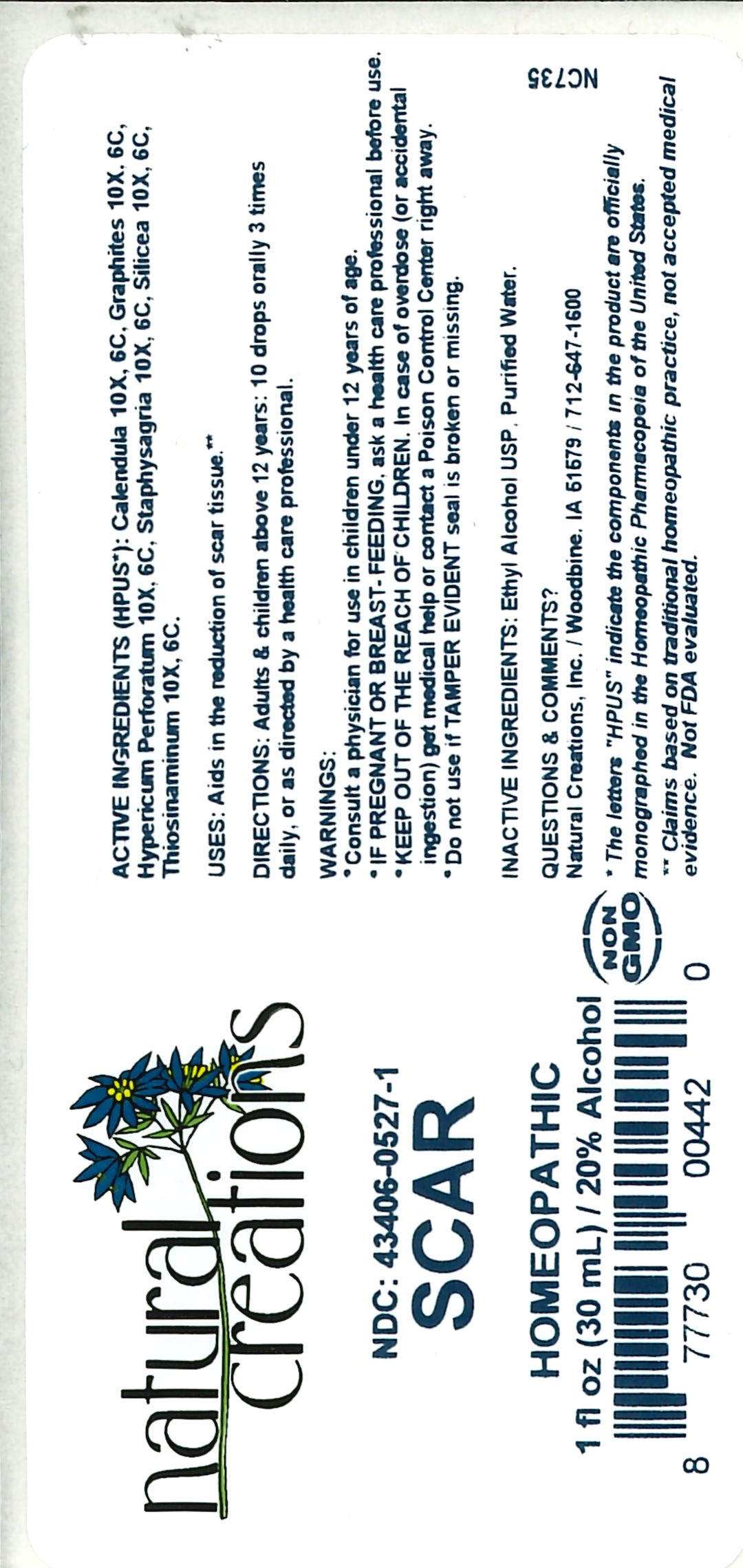 DRUG LABEL: Scar
NDC: 43406-0527 | Form: LIQUID
Manufacturer: Natural Creations, Inc
Category: homeopathic | Type: HUMAN OTC DRUG LABEL
Date: 20251216

ACTIVE INGREDIENTS: CALENDULA OFFICINALIS FLOWERING TOP 6 [hp_C]/1 mL; GRAPHITE 6 [hp_C]/1 mL; HYPERICUM PERFORATUM WHOLE 6 [hp_C]/1 mL; DELPHINIUM STAPHISAGRIA SEED 6 [hp_C]/1 mL; SILICON DIOXIDE 6 [hp_C]/1 mL; ALLYLTHIOUREA 6 [hp_C]/1 mL
INACTIVE INGREDIENTS: ALCOHOL; WATER

Scar

ACTIVE INGREDIENT

ACTIVE INGREDIENTS (HPUS*): Calendula 10X, 6C, Graphites 10X, 6C, Hypericum Perforatum 10X, 6C, Staphysagria 10X, 6C, Silicea 10X, 6C, Thiosinaminum 10X, 6C

INDICATIONS AND USAGE

USES: Aids in the reduction of scar tissue.**

PURPOSE

USES: Aids in the reduction of scar tissue.**

DOSAGE AND ADMINISTRATION

DIRECTIONS: Adults & children above 12 years: 10 drops orally 3 times daily, or as directed by a health care professional.

KEEP OUT OF REACH OF CHILDREN

KEEP OUT OF THE REACH OF CHILDREN. In case of overdose (or accidental ingestion) get medical help or contact a Poison Control Center right away.

WARNINGS:

- Consult a physician for use in children under 12 years of age.
- IF PREGNANT OR BREAST-FEEDING, ask a health care professional before use.
- KEEP OUT OF THE REACH OF CHILDREN. In case of overdose (or accidental ingestion) get medical help or contact a Poison Control Center right away.
- Do not use if TAMPER EVIDENT seal is broken or missing.

INACTIVE INGREDIENTS: Ethyl Alcohol USP, Purified Water

QUESTIONS & COMMENTS?

Natural Creations, Inc. / Woodbine, IA 51579 / 712-647-1600

REFERENCES

*The letters "HPUS" indicate the components in the product are officially monographed in the Homeopathic Pharmacopeia of the United States.

**Claims based on traditional homeopathic practice, not accepted medical evidence. Not FDA evaluated.

PACKAGE LABEL

NDC:43406-0527-1

Scar

HOMEOPATHIC

1 fl oz (30mL) / 20% Alcohol